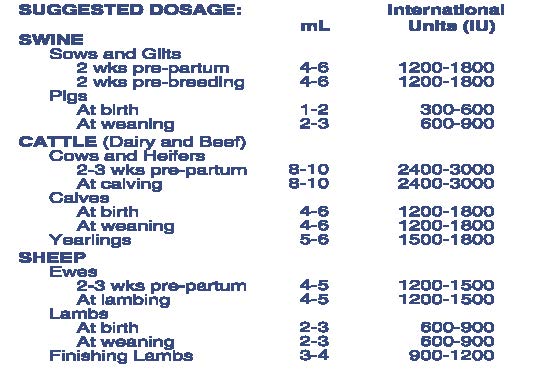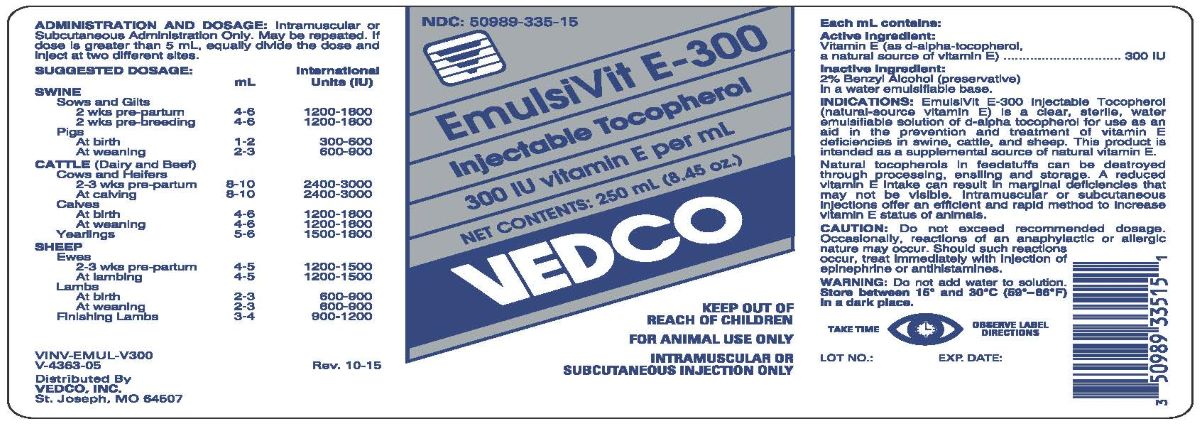 DRUG LABEL: EmulsiVit E-300
NDC: 50989-335 | Form: INJECTION
Manufacturer: Vedco, Inc.
Category: animal | Type: OTC ANIMAL DRUG LABEL
Date: 20240604

ACTIVE INGREDIENTS: .ALPHA.-TOCOPHEROL, D- 201 mg/1 mL

EmulsiVit E-300

INDICATIONS AND USAGE

Injectable Tocopherol

300 IU vitamin E per mL

Keep Out of Reach of Children

FOR ANIMAL USE ONLY

INTRAMUSCULAR OR SUBCUTANEOUS INJECTION ONLY

Each mL contains:

Active Ingredients:

vitamin E (as d-alpha-tocopherol,

a natural source of vitamin E).....................................300 IU

Inactive Ingredients: 2% Benzyl Alcohol (preservative) in a water emulsifiable base.

Caution:

Do not exceed recommended dosage.
Occasionally, reactions of an anaphylactic or allergic nature
may occur. Should such reactions occur, treat immediately
with injection of epinephrine or antihistamines.

Warning:

Do not add water to solution.

STORAGE AND HANDLING

Store between 15°—30°C (59°—86°F) in a dark place

ADMINISTRATION AND DOSAGE:

Intramuscular or Subcutaneous Administration Only. May be repeated. If dose is greater than 5 mL, equally divide the dose and inject at two sites.